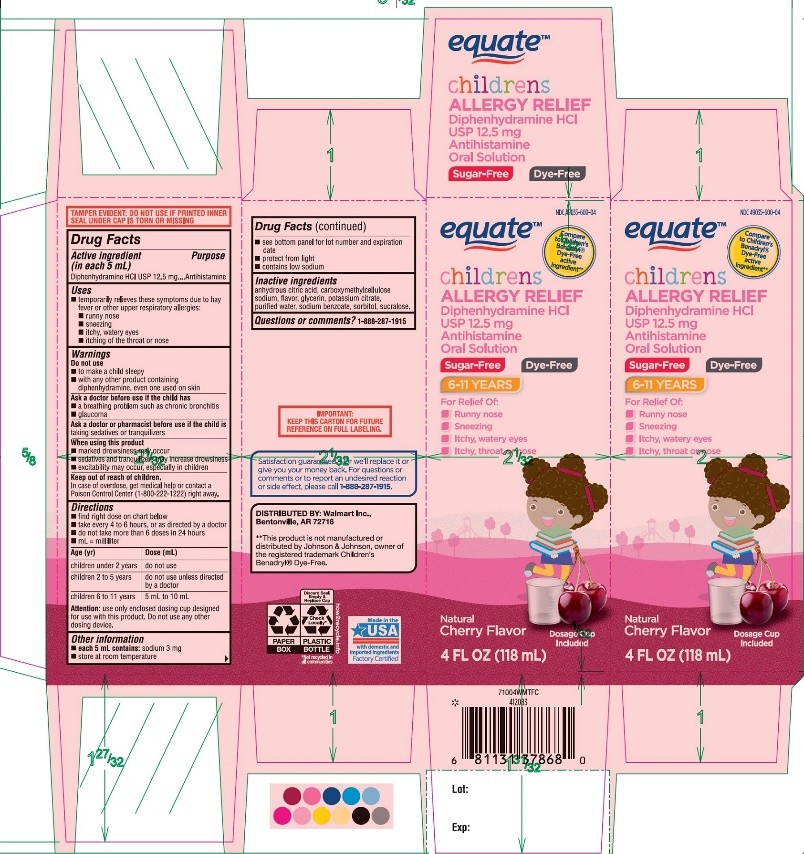 DRUG LABEL: Dye Free Childrens Allergy Relief
NDC: 49035-600 | Form: SOLUTION
Manufacturer: WAL-MART STORES INC.
Category: otc | Type: HUMAN OTC DRUG LABEL
Date: 20251027

ACTIVE INGREDIENTS: DIPHENHYDRAMINE HYDROCHLORIDE 12.5 mg/5 mL
INACTIVE INGREDIENTS: ANHYDROUS CITRIC ACID; CARBOXYMETHYLCELLULOSE SODIUM, UNSPECIFIED; GLYCERIN; POTASSIUM CITRATE; WATER; SODIUM BENZOATE; SORBITOL; SUCRALOSE

Dye-Free Children’s Allergy Relief Cherry Flavor 4 FL OZ 118 mL

Drug Facts

Active ingredient (in each 5 mL)

Diphenhydramine HCl USP 12.5 mg

Purpose

Antihistamine

Uses

- temporarily relieves these symptoms due to hay fever or other upper respiratory allergies:
  - Runny nose
  - Sneezing
  - Itchy, Watery Eyes
  - Itchy of the throat or Nose

Warnings

Do not use

- to make a child sleepy
- with any other product containing diphenhydramine, even one used on skin

Ask a doctor before use if the child has

- a breathing problem such as chronic bronchitis
- glaucoma

Ask a doctor or pharmacist before use if the child istaking sedatives or tranquilizers

When using this product

- marked drowsiness may occur
- sedatives and tranquilizers may increase drowsiness
- excitability may occur, especially in children

Keep out of reach of children.

In case of overdose, get medical help or contact a Poison Control Center right away. (1-800-222-1222)

Directions

- find right dose on chart below
- take every 4 to 6 hours, or as directed by a doctor
- do not take more than 6 doses in 24 hours
- mL = milliliter

Age (yr) | Dose (mL)
children under 2 years | do not use
children 2 to 5 years | do not use unless directed by a doctor
children 6 to 11 years | 5mL to 10 mL

Attention:use only enclosed dosing cup designed for use with this product. Do not use any other dosing device.

Other information

- each 5 mL contains:sodium 3 mg
- store at room temperature
- see bottom panel for lot number and expiration date
- protect from light
- contains low sodium

Inactive ingredients

anhydrous citric acid, carboxymethylcellulose sodium, flavors, glycerin, potassium citrate, purified water, sodium benzoate, sorbitol, sucralose.

Questions or comments?

1-888-287-1915

PRINCIPAL DISPLAY PANEL

*Compare to Children's Benadryl®Dye-Free active ingredient**

NDC 49035-600-04

Dye-Free

Children’s Allergy Relief

Diphenhydramine HCl USP 12.5 mg ǀ Antihistamine
Oral solution

For Relief of:

- Runny Nose,
- Sneezing
- Itchy, Watery Eyes
- Itchy Throat or Nose

Sugar-Free | Dye-Free

6-11 YEARS

Natural Cherry Flavor

4 FL OZ (118 mL)
TAMPER EVIDENT: DO NOT USE IF PRINTED INNER SEAL UNDER CAP IS TORN OR MISSING

*This product is not manufactured or distributed by Johnson and Johnson, owner of the registered trademark Children’s Benadryl®Dye–Free.

IMPORTANT:Keep this carton for the future reference on full labeling.

DISTRIBUTED BY:

Walmart Inc.,

Bentonville, AR 72716

Satisfaction guaranteed- Or we’ll replace it or give you your money back. For question or comments or to report an undesired reaction or side effect, please call 1-888-287-1915